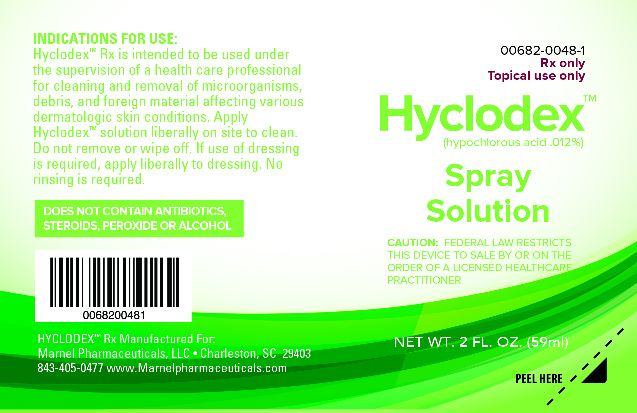 DRUG LABEL: Hyclodex
NDC: 00682-0048
Manufacturer: Marnel Pharmaceuticals, Inc.
Category: other | Type: PRESCRIPTION MEDICAL DEVICE LABEL
Date: 20180301

Hyclodex

INDICATIONS FOR USE:

HyclodexTM Rx is intented to be used under the supervison of a health care professional for cleaning and removal of microorganisms, debris, and foreign material affecting various dermatologic skin conditions. Apply HyclodexTM solution liberally on site to clean. Do not remove or wipe off. If use of dressing is required, apply liberally to dressing. No rinsing is required.

INFORMATION FOR OWNERS/CAREGIVERS

DOES NOT CONTAIN ANTIBIOTICS, STEROIDS, PEROXIDE OR ALCOHOL.

INFORMATION FOR OWNERS/CAREGIVERS

For Topical Use Only - Rx Only

SUMMARY OF SAFETY AND EFFECTIVENESS

PRODUCT SUMMARY: HyclodexTM is a proprietary skin solution containing balanced analytic hypochlorious acid as a preservative, which is known to be safe and fast acting in the removal of microorganisms of the skin.

CONTRAINDICATIONS

CONTRAINDICATIONS: Check for known hypersensitivity to any of the HyclodexTM solution ingredients.

INSTRUCTIONS FOR USE

DIRECTIONS OF USE: Spray HyclodexTM on a clean gauze pad. Thoroughly apply to affected areas and allow product to fully dry on skin. Apply product 2 times per day or as directed.

STORAGE AND HANDLING

STORAGE: Store at a controlled room temperature of 65ο to 75ο F. Keep away from direct sunlight and heat sources. Do Not Freeze.

Handling and Disposal: HyclodexTM is non-irritating, non-cytoxic and nonsensitizing to skin and eyes. Special handling or disposal precautions are not required.

SAFE HANDLING WARNING

SAFETY: HyclodexTM is non-irritating and nonsensitizing having passed bio-compatibility studies including, ISO ocular irritation and ISO Maximum Sensitivity test.

WARNINGS AND PRECAUTIONS: For external use only. Do not use for infusion or injection. Do not swallow. If you experience redness, swelling, irritation or pain, discontinue use and contact your doctor. In case of sensitivities to chlorine, please exercise caution and consult with your doctor prior to use. Do not use expired product. Keep out of reach of children.

HOW SUPPLIED

HOW SUPPLIED: HyclodexTM is available in 59 ml spray solution.